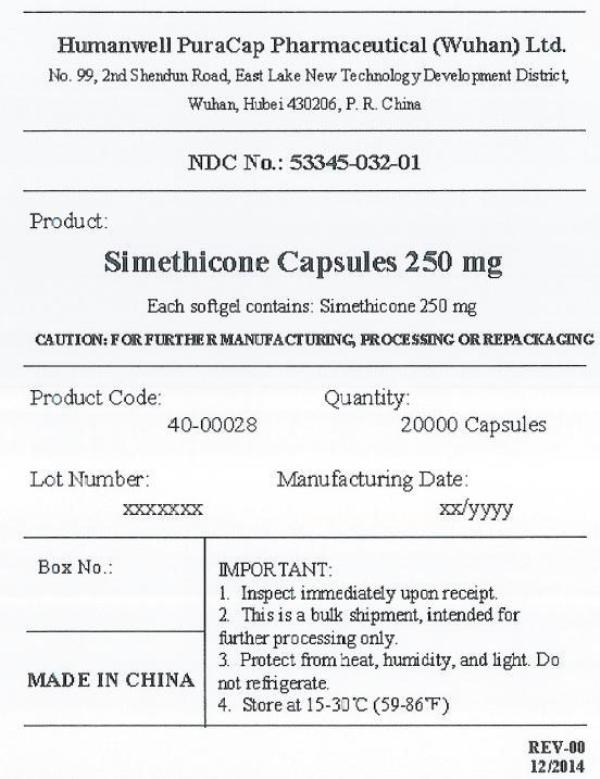 DRUG LABEL: Simethicone
NDC: 53345-032 | Form: CAPSULE, LIQUID FILLED
Manufacturer: Humanwell PuraCap Pharmaceutical (Wuhan) Co., Ltd.
Category: otc | Type: HUMAN OTC DRUG LABEL
Date: 20241121

ACTIVE INGREDIENTS: DIMETHICONE 250 mg/1 1
INACTIVE INGREDIENTS: FD&C BLUE NO. 1; FD&C RED NO. 40; GELATIN; GLYCERIN; WATER

SIMETHICONE CAPSULES 250 mg, liquid filled

Active ingredient (in each capsule)

Simethicone 250 mg

Purpose

Anti-gas

Uses

- relieves bloating, pressure or fullness commonly referred to as gas

Warnings

Stop use and ask a doctor if

condition persists

Keep out of reach of children.

Directions

- swallow one or two softgels after a meal
- do not exceed two softgels per 24 hours except under the advice and supervision of a physician

Other information

- store at room temperature 59°-86°F (15°-30°C)

Inactive ingredients

FD&C Blue #1, FD&C Red #40, gelatin, glycerin, purified water, and white edible ink

Manufactured by:
Humanwell PuraCap Pharmaceutical (Wuhan) Co., Ltd.
Wuhan, Hubei
430206, China

PRINCIPAL DISPLAY PANEL - Shipping Label

SIMETHICONE CAPSULES, 250 mg

Quantity : 25000 Capsules
NDC. No : 53345-032-01

IMPORTANT:
1.Inspect immediate upon receipt.
2.This is a bulk shipment, intended for further processing only.
3.Protect from heat, humidity, and light. Do not refrigerate.
4.Store at 15-30°C (59-86°F)

CAUTION : FOR FURTHER MANUFACTURING, PROCESSING OR REPACKAGING